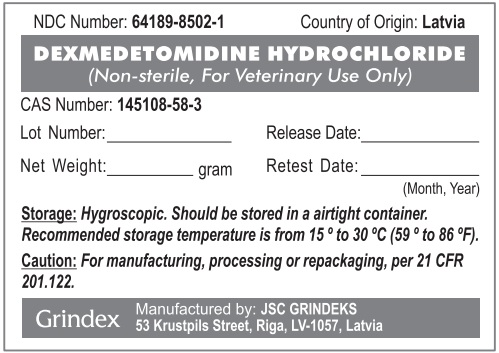 DRUG LABEL: Dexmedetomidine Hydrochloride
NDC: 64189-8502 | Form: POWDER
Manufacturer: GRINDEKS Joint Stock Company
Category: other | Type: BULK INGREDIENT - ANIMAL DRUG
Date: 20251216

ACTIVE INGREDIENTS: DEXMEDETOMIDINE HYDROCHLORIDE 1 g/1 g

Dexmedetomidine Hydrochloride

WARNINGS AND PRECAUTIONS

Caution: For manufacturing, processing, or repackaging, per 21 CFR 201.122.

STORAGE AND HANDLING

Storage: Hygroscopic. Should be stored in a airtight container. Recommended storage temperature is from 15° to 30°C (59° to 86°F).

PACKAGE LABEL

NDC Number: 64189-8502-1 Country of Origin: Latvia

DEXMEDETOMIDINE HYDROCHLORIDE

(Non-sterile, For Veterinary Use Only)

Cas Number: 145108-58-3

Lot Number:_______________ Release Date:____________

Net Weight:____________gram Retest Date:_____________ (Month, Year)

Storage: Hygroscopic. Should be stored in a airtight container. Recommended storage temperature is from 15° to 30°C (59° to 86°F).

Caution: For manufacturing, processing, or repackaging, per 21 CFR 201.122.

Grindex

Manufactured by: JSC GRINDEKS

53 Krustpils Street, Riga, LV-1057, Latvia